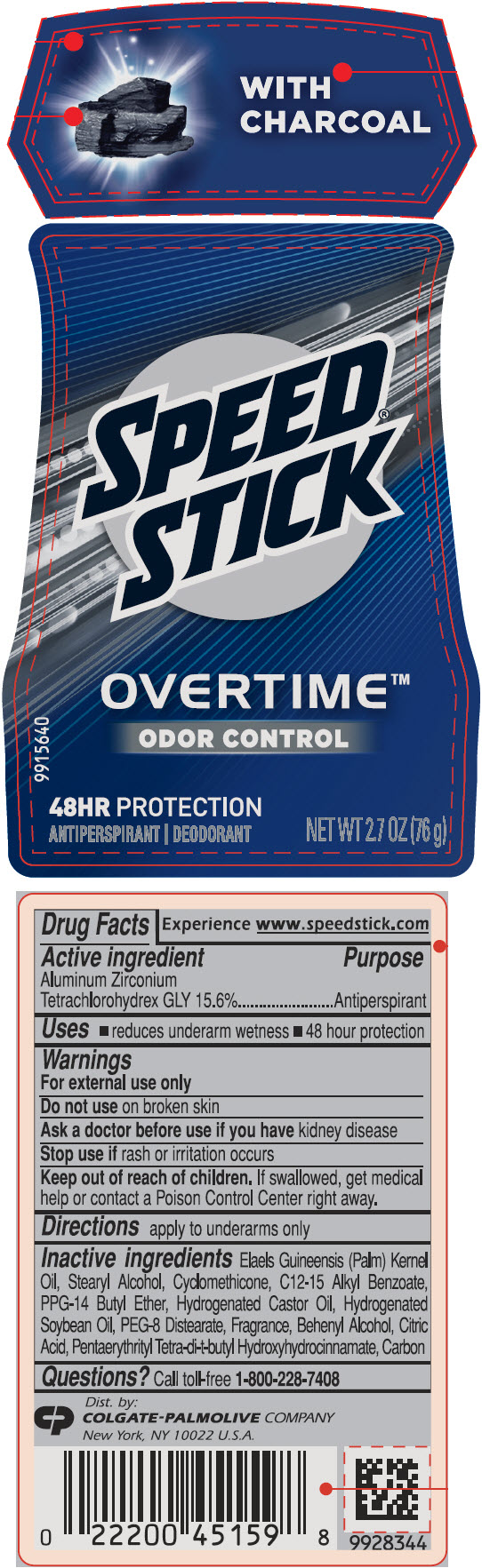 DRUG LABEL: Mens Speed Overtime Odor Control with Charcoal - antiperspirant/deodorant
NDC: 35000-694 | Form: STICK
Manufacturer: COLGATE PALMOLIVE COMPANY
Category: otc | Type: HUMAN OTC DRUG LABEL
Date: 20210525

ACTIVE INGREDIENTS: ALUMINUM ZIRCONIUM TETRACHLOROHYDREX GLY 156 mg/1 g
INACTIVE INGREDIENTS: PALM KERNEL OIL; STEARYL ALCOHOL; CYCLOMETHICONE; ALKYL (C12-15) BENZOATE; PPG-14 BUTYL ETHER; HYDROGENATED CASTOR OIL; HYDROGENATED SOYBEAN OIL; PEG-8 DISTEARATE; DOCOSANOL; CITRIC ACID MONOHYDRATE; PENTAERYTHRITOL TETRAKIS(3-(3,5-DI-TERT-BUTYL-4-HYDROXYPHENYL)PROPIONATE); ACTIVATED CHARCOAL

Mens Speed® Stick Overtime Odor Control with Charcoal - antiperspirant/deodorant

Drug Facts

Active ingredient

Aluminum Zirconium Tetrachlorohydrex GLY 15.6%

Purpose

Antiperspirant

Uses

- reduces underarm wetness
- 48 hour protection

Warnings

For external use only

Do not use on broken skin

Ask a doctor before use if you have kidney disease

Stop use if rash or irritation occurs

Keep out of reach of children. If swallowed, get medical help or contact a Poison Control Center right away.

Directions

apply to underarms only

Inactive ingredients

Elaels Guineensis (Palm) Kernel Oil, Stearyl Alcohol, Cyclomethicone, C12-15 Alkyl Benzoate, PPG-14 Butyl Ether, Hydrogenated Castor Oil, Hydrogenated Soybean Oil, PEG-8 Distearate, Fragrance, Behenyl Alcohol, Citric Acid, Pentaerythrityl Tetra-di-t-butyl Hydroxyhydrocinnamate, Carbon

Questions?

Call toll-free 1-800-228-7408

Dist. by:
COLGATE-PALMOLIVE COMPANY
New York, NY 10022 U.S.A.

PRINCIPAL DISPLAY PANEL - 76 g Container Label

WITH
CHARCOAL

SPEED®
STICK

OVERTIME™
ODOR CONTROL

48HR PROTECTION

ANTIPERSPIRANT | DEODORANT

NET WT 2.7 OZ (76 g)

9915640